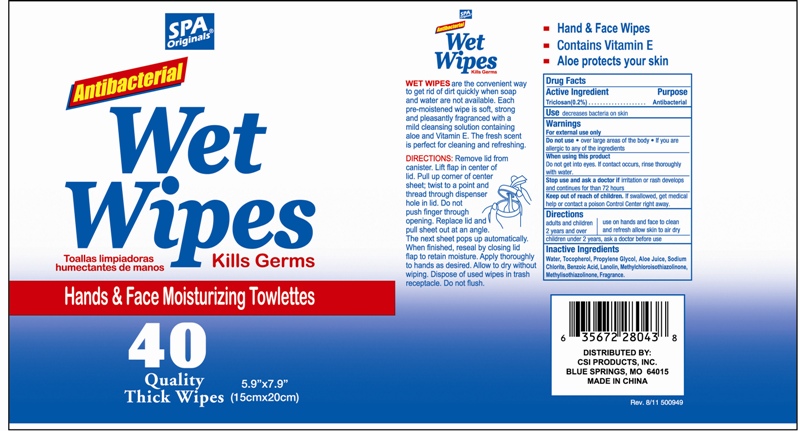 DRUG LABEL: Antibacterial Wet Wipes
NDC: 42856-001 | Form: SWAB
Manufacturer: MAKESELLER GROUP INC. 
Category: otc | Type: HUMAN OTC DRUG LABEL
Date: 20120312

ACTIVE INGREDIENTS: Triclosan 0.2 g/100 g
INACTIVE INGREDIENTS: WATER; Tocopherol; Propylene Glycol; Aloe; Sodium Chlorite; Benzoic Acid; Lanolin; METHYLCHLOROISOTHIAZOLINONE ; METHYLISOTHIAZOLINONE

Antibacterial Wet Wipes Hand &Face Moisturizing Towlettes Hank &Face Wipes Contains Vitamin E Aloe Protects your skin

Active Ingredient

Triclosan(0.2%)

Purpose

Antibacterial

Use

decreases bacteria on skin

WARNINGS

For External use only.
Do not use
.over large areas of the body
.if your are allergic to any of the ingredients
When using this product
Do not get into eyes,if contact occurs ,rinse throughly with water.
Stop use and ask a doctor,if irritation or rash develops and continues for than 72 hours

keep out of reach of children

if swallowed ,get medical help or contact o poison Control Center right away

Directions

Adults and children 2 years and over:use on hands and face to clean and refresh allow skin to air dry.
Children under 2 years ,ask a doctor before use

Inactive ingredients

WATER,Tocopherol,Propylene Glycol,Aloe,Sodium Chlorite,Benzoic Acid,Lanolin, METHYLCHLOROISOTHIAZOLINONE , METHYLISOTHIAZOLINONE

PACKAGE LABEL

section text here